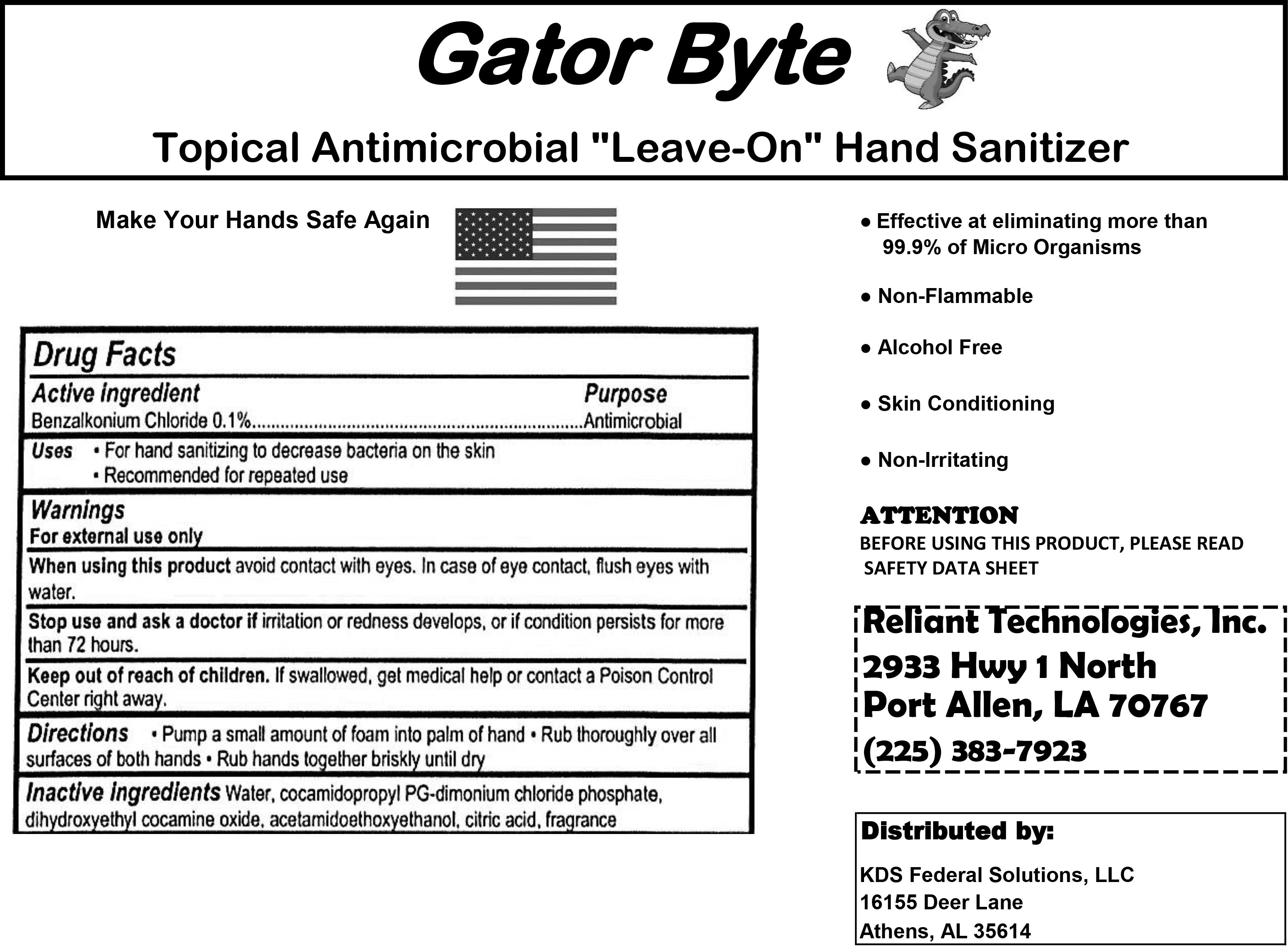 DRUG LABEL: Gator Byte
NDC: 78094-001 | Form: LIQUID
Manufacturer: Reliant Technologies
Category: otc | Type: HUMAN OTC DRUG LABEL
Date: 20200518

ACTIVE INGREDIENTS: BENZALKONIUM CHLORIDE 1.05 g/1000 g
INACTIVE INGREDIENTS: CETRIMONIUM CHLORIDE 0.66 g/1000 g; GLYCERETH-17 COCOATE 0.5 g/1000 g; ANHYDROUS CITRIC ACID 0.02 g/1000 g; LAURTRIMONIUM CHLORIDE 0.5 g/1000 g; WATER 996.82 g/1000 g; DIHYDROXYETHYL COCAMINE OXIDE 0.45 g/1000 g

Non-Alcohol Hand Sanitizer

Active Ingredient

Benzalkonium Chloride 0.1%

Warnings

Warnings Section

Inactive Ingredients

Inactive ingredients section

Usage and Indications section

Keep Out of Reach of Children section

Purpose Section

Under purpose next to active ingredients

Packaging Label

3785 mL (1 gallon) NDC: 78094-3740-1